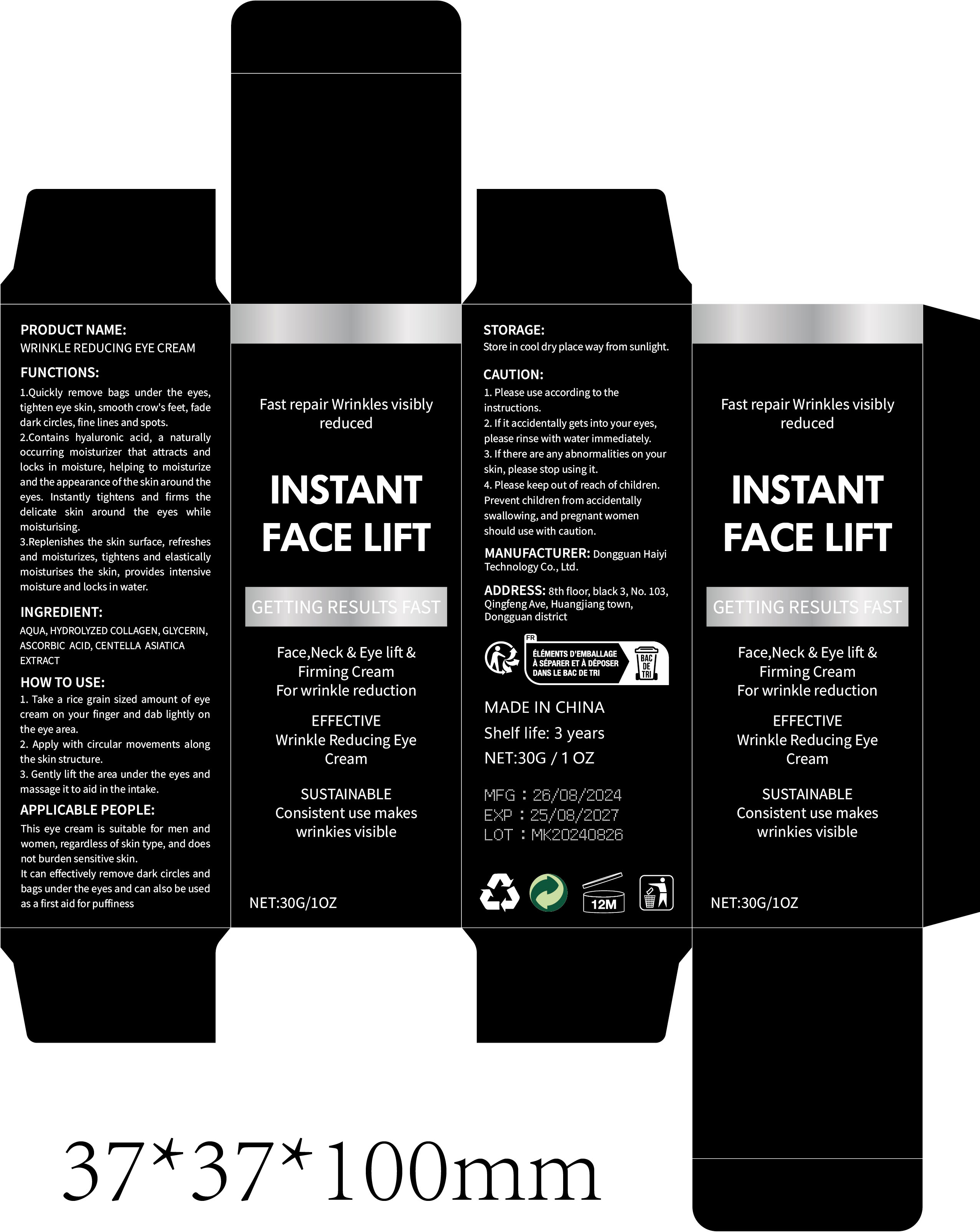 DRUG LABEL: WRINKLE REDUCING EYE Cream
NDC: 84732-046 | Form: CREAM
Manufacturer: Dongguan Haiyi Technology Co.,Ltd.
Category: otc | Type: HUMAN OTC DRUG LABEL
Date: 20241014

ACTIVE INGREDIENTS: CENTELLA ASIATICA TRITERPENOIDS 1 mg/100 g
INACTIVE INGREDIENTS: PENICILLOYL POLYLYSINE; ASCORBIC ACID; GLYCERIN; WATER

Active ingredient

CENTELLA ASIATICA EXTRACT

Inactive ingredient

AQUA, HYDROLYZED COLLAGEN, GLYCERIN,ASCORBIC ACID

Purpose section

1.Quickly remove bags under the eyes,tighten eye skin, smooth crow's feet, fadedark circles, fine lines and spots.

2.Contains hyaluronic acid, a naturallyoccurring moisturizer that attracts andlocks in moisture, helping to moisturizeand the appearance ofthe skin around theeyes. Instantly tightens and firms thedelicate skin around the eyes whilemoisturising

3.Replenishes the skin surface, refreshesand moisturizes, tightens and elasticallymoisturises the skin, provides intensivemoisture and locks in water.

Warning

1. Please use according to the instructions.
2. lf it accidentally gets into your eyes,please rinse with water immediately.

3. lf there are any abnormalities on yourskin, please stop using it.

4. Please keep out of reach of children.Prevent children from accidentallyswallowing,and pregnant womenshould use with caution.

stop use

This product may cause allergic reactions in asmall number of people.
lf you experience any discomfort,please stop using it immediately.

not use

Not suitable for use by children, pregnantor breast feeding people.

OUT OF CHILDREN

KEEP THE PRODUCT OUT OF REACH OF CHILDREN to

HOW TO USE

1. Take a rice grain sized amount of eyecream on your finger and dab lightly onthe eye area.

2. Apply with circular movements alongthe skin structure.

3. Gently lift the area under the eyes andmassage it to aid in the intake.

Dosage

take an appropriateamount,Use 2-3 times a week